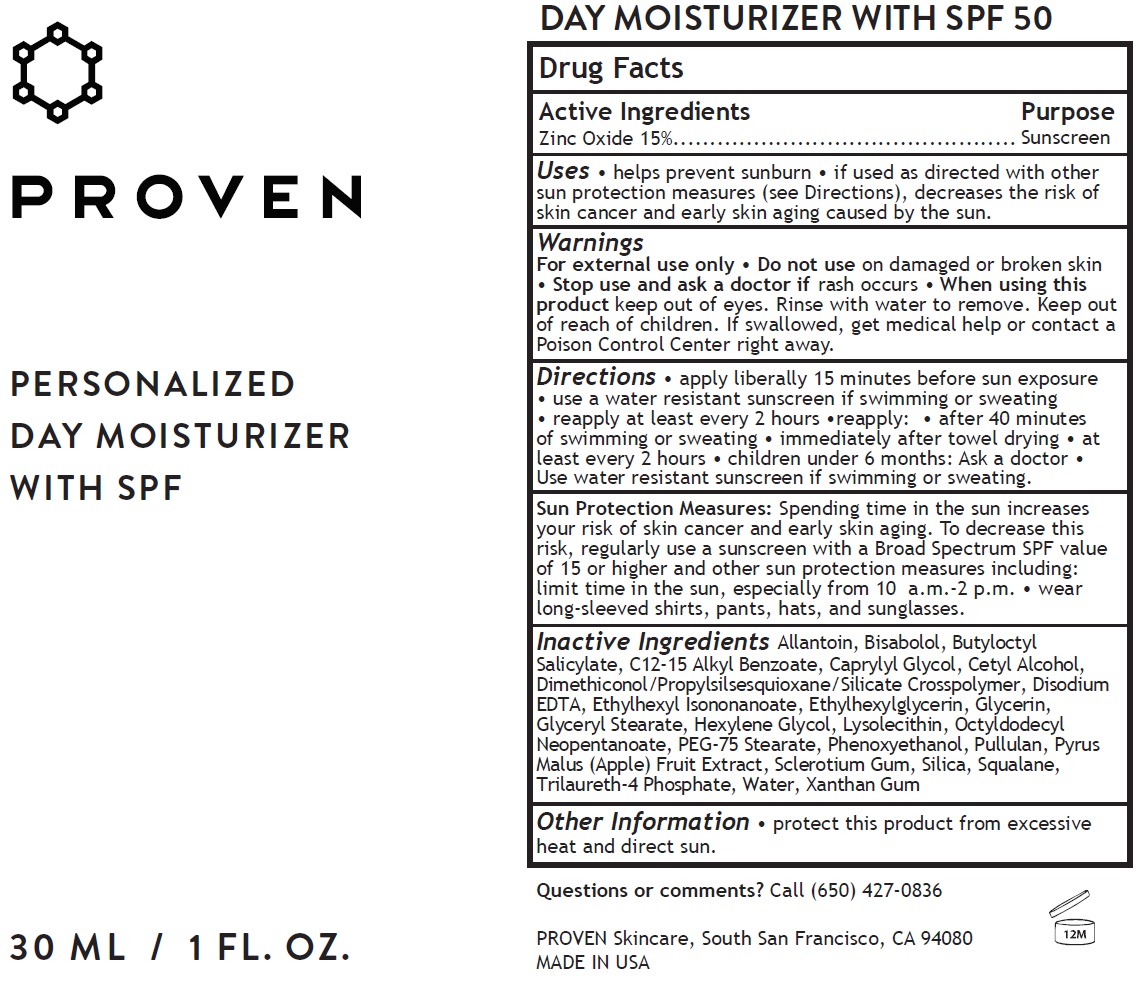 DRUG LABEL: Proven Personalized Day Moisturizer With SPF 50
NDC: 73572-004 | Form: CREAM
Manufacturer: Proven Skincare
Category: otc | Type: HUMAN OTC DRUG LABEL
Date: 20231110

ACTIVE INGREDIENTS: ZINC OXIDE 150 mg/1 mL
INACTIVE INGREDIENTS: ALLANTOIN; LEVOMENOL; BUTYLOCTYL SALICYLATE; ALKYL (C12-15) BENZOATE; CAPRYLYL GLYCOL; CETYL ALCOHOL; DIMETHICONOL/PROPYLSILSESQUIOXANE/SILICATE CROSSPOLYMER (450000000 MW); EDETATE DISODIUM ANHYDROUS; ETHYLHEXYL ISONONANOATE; ETHYLHEXYLGLYCERIN; GLYCERIN; GLYCERYL MONOSTEARATE; HEXYLENE GLYCOL; LYSOPHOSPHATIDYLCHOLINE, SOYBEAN; OCTYLDODECYL NEOPENTANOATE; PEG-75 STEARATE; PHENOXYETHANOL; PULLULAN; APPLE; BETASIZOFIRAN; SILICON DIOXIDE; SQUALANE; TRILAURETH-4 PHOSPHATE; WATER; XANTHAN GUM

Proven Personalized Day Moisturizer With SPF 50

Active Ingredients

Zinc Oxide 15%

Purpose

Sunscreen

Uses

• helps prevent sunburn • if used as directed with other sun protection measures (see Directions), decreases the risk of skin cancer and early skin aging caused by the sun.

Warnings

For external use only

Do not use

- on damaged or broken skin

Stop use and ask a doctor

- if rash occurs

When using this product

- keep out of eyes. Rinse with water to remove.

Keep out of reach of children.

If swallowed, get medical help or contact a Poison Control Center right away.

Directions

• apply liberally 15 minutes before sun exposure • use a water resistant sunscreen if swimming or sweating • reapply at least every 2 hours •reapply: • after 40 minutes of swimming or sweating • immediately after towel drying • at least every 2 hours • children under 6 months: Ask a doctor • Use water resistant sunscreen if swimming or sweating.

Spending time in the sun increases your risk of skin cancer and early skin aging. To decrease this risk, regularly use a sunscreen with a Broad Spectrum SPF value of 15 or higher and other sun protection measures including: limit time in the sun, especially from 10 a.m.-2 p.m. • wear long-sleeved shirts, pants, hats, and sunglasses. Sun Protection Measures:

Inactive Ingredients

Allantoin, Bisabolol, Butyloctyl Salicylate, C12-15 Alkyl Benzoate, Caprylyl Glycol, Cetyl Alcohol, Dimethiconol/Propylsilsesquioxane/Silicate Crosspolymer, Disodium EDTA, Ethylhexyl Isononanoate, Ethylhexylglycerin, Glycerin, Glyceryl Stearate, Hexylene Glycol, Lysolecithin, Octyldodecyl Neopentanoate, PEG-75 Stearate, Phenoxyethanol, Pullulan, Pyrus Malus (Apple) Fruit Extract, Sclerotium Gum, Silica, Squalane, Trilaureth-4 Phosphate, Water, Xanthan Gum

Other Information

• protect this product from excessive heat and direct sun.

Questions or comments?

Call (650) 427-0836